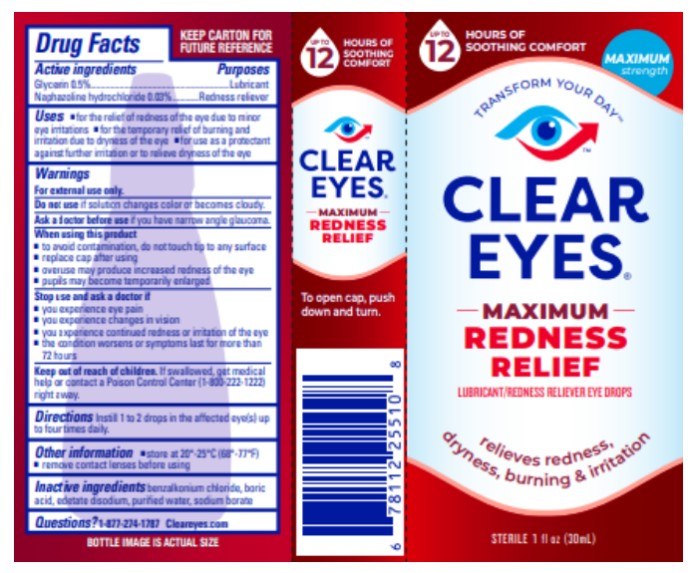 DRUG LABEL: Clear Eyes Maximum Redness Relief
NDC: 67172-696 | Form: LIQUID
Manufacturer: Prestige Brands Holdings, Inc.
Category: otc | Type: HUMAN OTC DRUG LABEL
Date: 20250228

ACTIVE INGREDIENTS: NAPHAZOLINE HYDROCHLORIDE 0.3 mg/1 mL; GLYCERIN 5 mg/1 mL
INACTIVE INGREDIENTS: BENZALKONIUM CHLORIDE; BORIC ACID; EDETATE DISODIUM; WATER; SODIUM BORATE

Clear Eyes Max Redness Relief

Drug Facts

Active ingredients

Glycerin 0.5%

Purpose

Lubricant

Active ingredients

Naphazoline hydrochloride 0.03%

Purpose

Redness Reliever

Uses

- for the relief of redness of the eye due to minor eye irritations
- for the temporary relief of burning and irritation due to the dryness of the eye
- for use as a protectant against further irritation or dryness of the eye

Warnings

For external use only.

Do not use

if solution changes color or becomes cloudy.

Ask a doctor before use if

you have narrow angle glaucoma.

When using this product

- to avoid contamination, do not touch tip of container to any surface
- replace cap after using
- overuse may produce increased redness of the eye
- pupils may become temporarily enlarged

Stop use & ask a doctor if:

- you experience eye pain
- you experience changes in vision
- you experience continued redness or irritation of the eye
- the condition worsens or symptoms last for more than 72 hours

Keep out of reach of children.

If swallowed, get medical help or contact a Poison Control Center (1-800-222-1222) right away.

Directions

Instill 1 to 2 drops in the affected eye(s) up to four times daily.

Other information

- store at 20°-25°C (68°-77°F)
- remove contact lenses before using

Inactive ingredients

benzalkonium chloride, boric acid, edetate disodium, purified water, sodium borate

Questions?

1-877-274-1787 www.cleareyes.com

PRINCIPAL DISPLAY PANEL

CLEAR EYES®
MAXIMUM
REDNESS RELIEF
LUBRICANT/REDNESS RELIEVER EYE DROPS
STERILE 1 FL OZ (30 mL)